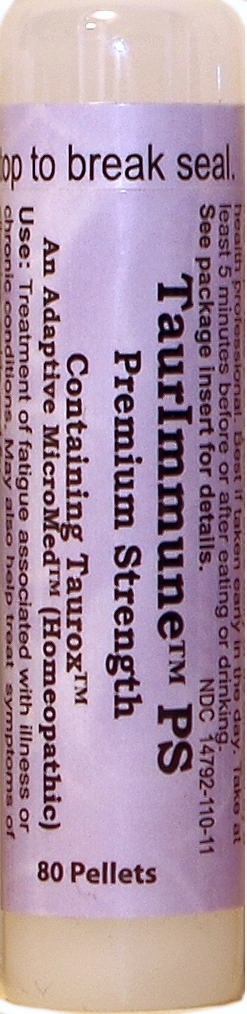 DRUG LABEL: TaurImmune PS
NDC: 73311-110 | Form: PELLET
Manufacturer: CureImmune
Category: homeopathic | Type: HUMAN OTC DRUG LABEL
Date: 20250128

ACTIVE INGREDIENTS: ZINC CARBOBENZOXY-.BETA.-ALANYLTAURINATE 6 [hp_X]/1 1
INACTIVE INGREDIENTS: SUCROSE; LACTOSE, UNSPECIFIED FORM

Taurimmune PS

Active Ingredients

Tauroxicum (COBAT) 3X (26%), 6X (37%), 9X (37%)

Use

For treatment of moderate to severe fatigue due to illness or chronic conditions. Immune support. May also help treat symptoms of colds, flu and allergies.

PURPOSE

For treatment of moderate to severe fatigue due to illness or chronic conditions. Immune support. May also help treat symptoms of colds, flu and allergies.

Directions

Directions for adults and children 15 years of age and older: Dissolve one to three pellets under tongue once daily, or as directed by a health professional. Best if taken early in the day, at least 5 minutes before or after eating. See package insert for details.

Warnings

Keep out of reach of children. Do not use if you are pregnant or breast feeding, an organ recipient, using immunosuppressive drugs, or if the tamper-evident seal is broken or missing. See package insert for details.

Keep out of reach of children.

Inactive Ingredients

Sucrose (80%), Lactose (20%).

Disclaimer

Claims based on traditional
homeopathic practice, not accepted
medical evidence. Not FDA evaluated.

PACKAGE LABEL

TaurImmune

PS

Premium Strength